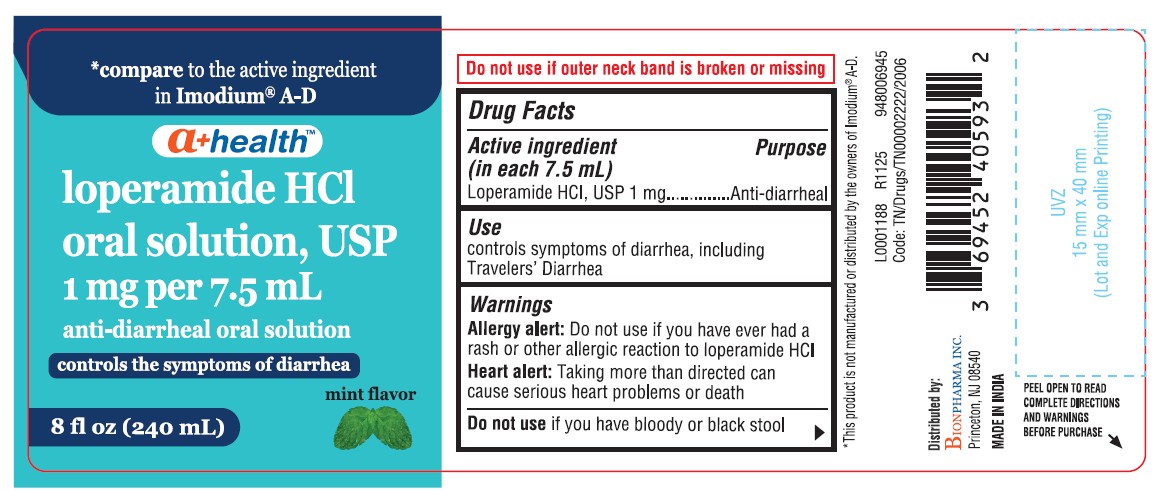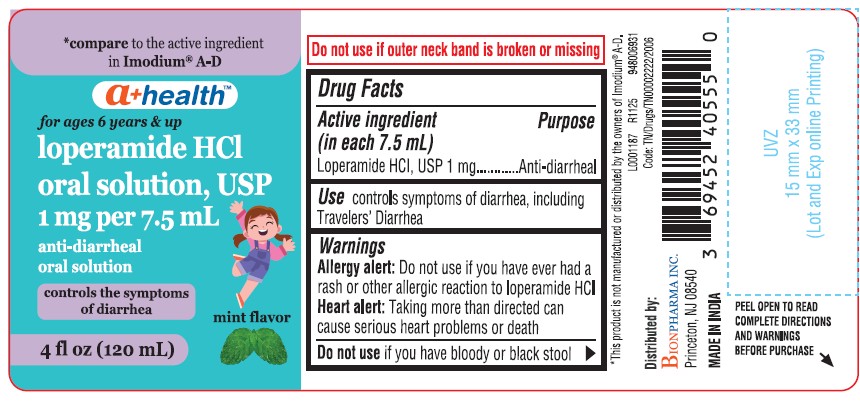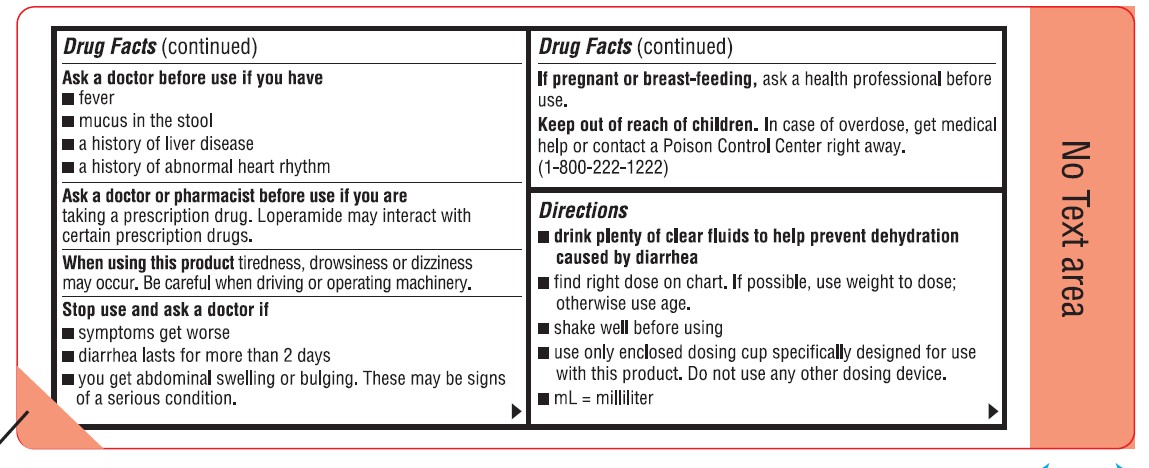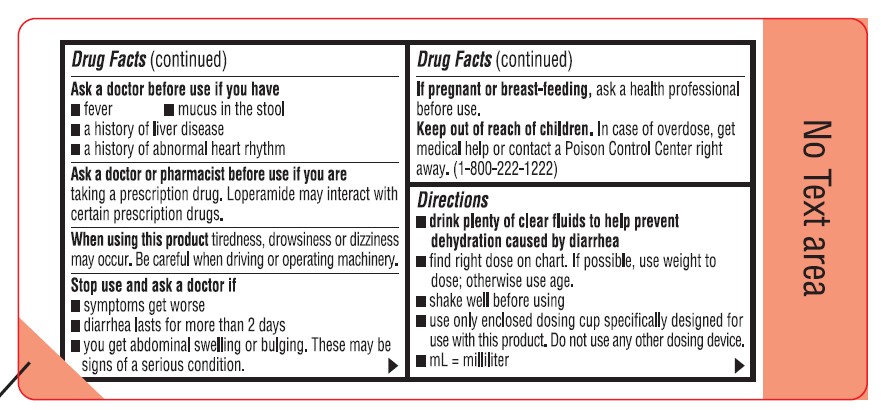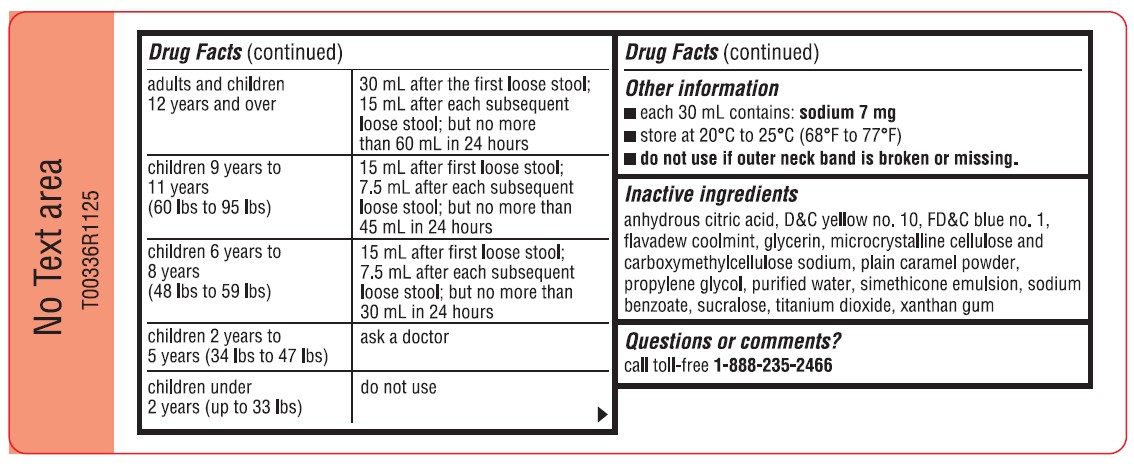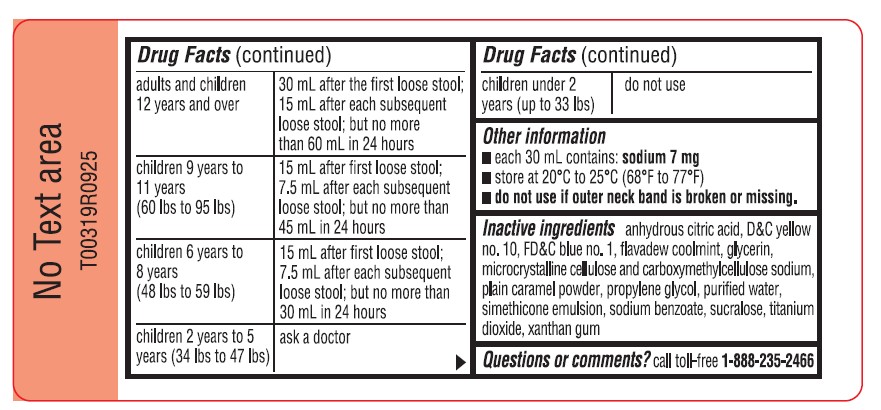 DRUG LABEL: Loperamide Hydrochloride
NDC: 69452-405 | Form: SOLUTION
Manufacturer: Bionpharma Inc.
Category: otc | Type: HUMAN OTC DRUG LABEL
Date: 20260227

ACTIVE INGREDIENTS: LOPERAMIDE HYDROCHLORIDE 1 mg/7.5 mL
INACTIVE INGREDIENTS: ANHYDROUS CITRIC ACID; D&C YELLOW NO. 10; FD&C BLUE NO. 1; GLYCERIN; MICROCRYSTALLINE CELLULOSE; CARBOXYMETHYLCELLULOSE SODIUM, UNSPECIFIED FORM; CARAMEL; PROPYLENE GLYCOL; WATER; DIMETHICONE; SODIUM BENZOATE; SUCRALOSE; TITANIUM DIOXIDE; XANTHAN GUM

a+ health-Loperamide HCL Oral Solution, USP

Drug Facts

Active ingredient (in each 7.5 mL)

Loperamide HCl, USP 1 mg

Purpose

Anti-diarrheal

Use

controls symptoms of diarrhea, including Travelers' Diarrhea

Warnings

Allergy alert:Do not use if you have ever had a rash or other allergic reaction to loperamide HCl

Heart alert:Taking more than directed can cause serious heart problems or death

DO NOT USE

Do not useif you have bloody or black stool

Ask a doctor before use if you have

- fever
- mucus in the stool
- a history of liver disease
- a history of abnormal heart rhythm

Ask a doctor or pharmacist before use if you are taking a prescription drug. Loperamide may interact with certain prescription drugs.

When using this product tiredness, drowsiness or dizziness may occur. Be careful when driving or operating machinery.

Stop use and ask a doctor if

- symptoms get worse
- diarrhea lasts for more than 2 days
- you get abdominal swelling or bulging. These may be signs of a serious condition.

PREGNANCY OR BREAST FEEDING

If pregnant or breast-feeding,ask a health professional before use.

Keep out of reach of children.In case of overdose, get medical help or contact a Poison Control Center right away. (1-800-222-1222)

Directions

- drink plenty of clear fluids to help prevent dehydration caused by diarrhea
- find right dose on chart. If possible, use weight to dose; otherwise use age.
- shake well before using
- use only enclosed dosing cup specifically designed for use with this product. Do not use any other dosing device.
- mL = milliliter

adults and children 12 years and over | 30 mL after the first loose stool; 15 mL after each subsequent loose stool; but no more than 60 mL in 24 hours
children 9 years to 11 years (60 lbs to 95 lbs) | 15 mL after first loose stool; 7.5 mL after each subsequent loose stool; but no more than 45 mL in 24 hours
children 6 years to 8 years (48 lbs to 59 lbs) | 15 mL after first loose stool; 7.5 mL after each subsequent loose stool; but no more than 30 mL in 24 hours
children 2 years to 5 years (34 lbs to 47 lbs) | ask a doctor
children under 2 years (up to 33 lbs) | do not use

Other information

- each 30 mL contains: sodium 7 mg
- store at 20°C to 25°C (68°F to 77°F)
- do not use if outer neck band is broken or missing.

Inactive ingredients

anhydrous citric acid, D&C yellow no. 10, FD&C blue no. 1, flavadew coolmint, glycerin, microcrystalline cellulose and carboxymethylcellulose sodium, plain caramel powder, propylene glycol, purified water, simethicone emulsion, sodium benzoate, sucralose, titanium dioxide, xanthan gum

Questions or comments?

call toll-free 1-888-235-2466

Do not use if outer neck band is broken or missing

PEEL OPEN TO READ COMPLETE DIRECTIONS AND WARNINGS BEFORE PURCHASE

*This product is not manufactured or distributed by the owners of Imodium®A-D.

Code: TN/Drugs/TN00002222/2006

L0001188 R1125 948006945

Distributed by:

BIONPHARMA INC.
Princeton, NJ 08540

MADE IN INDIA

PRINCIPAL DISPLAY PANEL-8 fl oz

*Compare to the active ingredient in Imodium®A-D

a+ healthTM

Loperamide HCl Oral Solution, USP
1 mg per 7.5 mL

Anti-Diarrheal Oral Solution

Controls the symptoms of diarrhea

Mint Flavor

8 fl oz (240 mL)

PRINCIPAL DISPLAY PANEL-4 fl oz

* Compare to the active ingredient in Imodium ®A-D

a+ healthTM

for ages 6 years & up

Loperamide HCl Oral Solution, USP

1 mg per 7.5 mL

Anti-Diarrheal Oral Solution

Controls the symptoms of diarrhea

Mint Flavor

4 fl oz (120 mL)